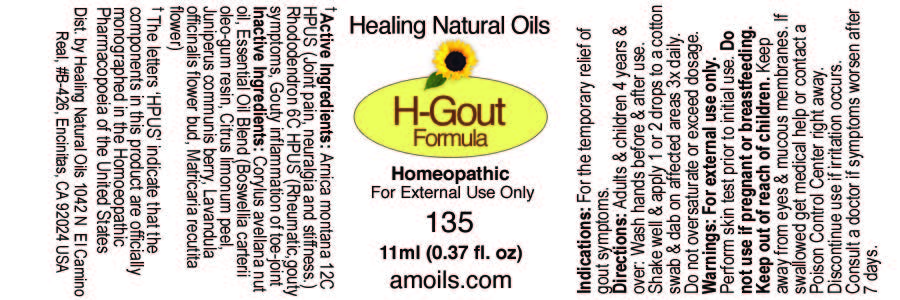 DRUG LABEL: H-Gout Formula
NDC: 61077-135 | Form: OIL
Manufacturer: Healing Natural Oils LLC
Category: homeopathic | Type: HUMAN OTC DRUG LABEL
Date: 20241211

ACTIVE INGREDIENTS: ARNICA MONTANA 12 [hp_C]/11 mL; RHODODENDRON AUREUM LEAF 6 [hp_C]/11 mL
INACTIVE INGREDIENTS: EUROPEAN HAZELNUT OIL; FRANKINCENSE OIL; LEMON JUICE; JUNIPER BERRY OIL; LAVANDULA ANGUSTIFOLIA FLOWERING TOP; CHAMOMILE FLOWER OIL

Active Ingredients:

Arnica Montana 12C HPUS, Rhododendron 6C HPUS

Purpose

Arnica Montana 12C HPUS (join pain, neuralgia and stiffness), Rhododendron 6C HPUS (Rheumatic, gouty symptoms, Gouty inflammation of toe-joint)

The letters ‘HPUS’ indicate that the components in this product are officially monographed in the Homoeopathic Pharmacopoeia of the United States

Inactive Ingredients:

Corylus avellana nut oil, Essential Oil Blend (Boswellia carterii oleo-gum resin, Citrus limonum peel, Juniperus communis berry, Lavandula officinalis flower bud, Matricaria recutita flower)

Indications:

For the temporary relief of gout symptoms.

Directions:

Adults and Children 4 years and over: Wash hands before and after use. Shake well and apply 1 or 2 drops to a cotton swab and dab on affected areas 3x daily. Do not oversaturate or exceed dosage.

Warnings:

For external use only.
Perform skin test prior to initial use.

Do not use if pregnant or breastfeeding.

Keep out of reach of children.

OTHER SAFETY INFORMATION

Keep away from eyes and mucous membranes. If swallowed get medical help or contact a Poison Control
Center right away.

Discontinue use if irritation occurs.

ASK DOCTOR

Consult a doctor if symptoms worsen after 7 days.

DESCRIPTION

Dist. by Healing Natural Oils 1041 N El Camino Real, #B-426, Encinitas, CA 92024 USA

Principal Display Panel

HealingNatural Oils

H-Gout
Formula
Homeopathic
For External Use Only
135
11ml (0.37 fl. oz)

amoils.com